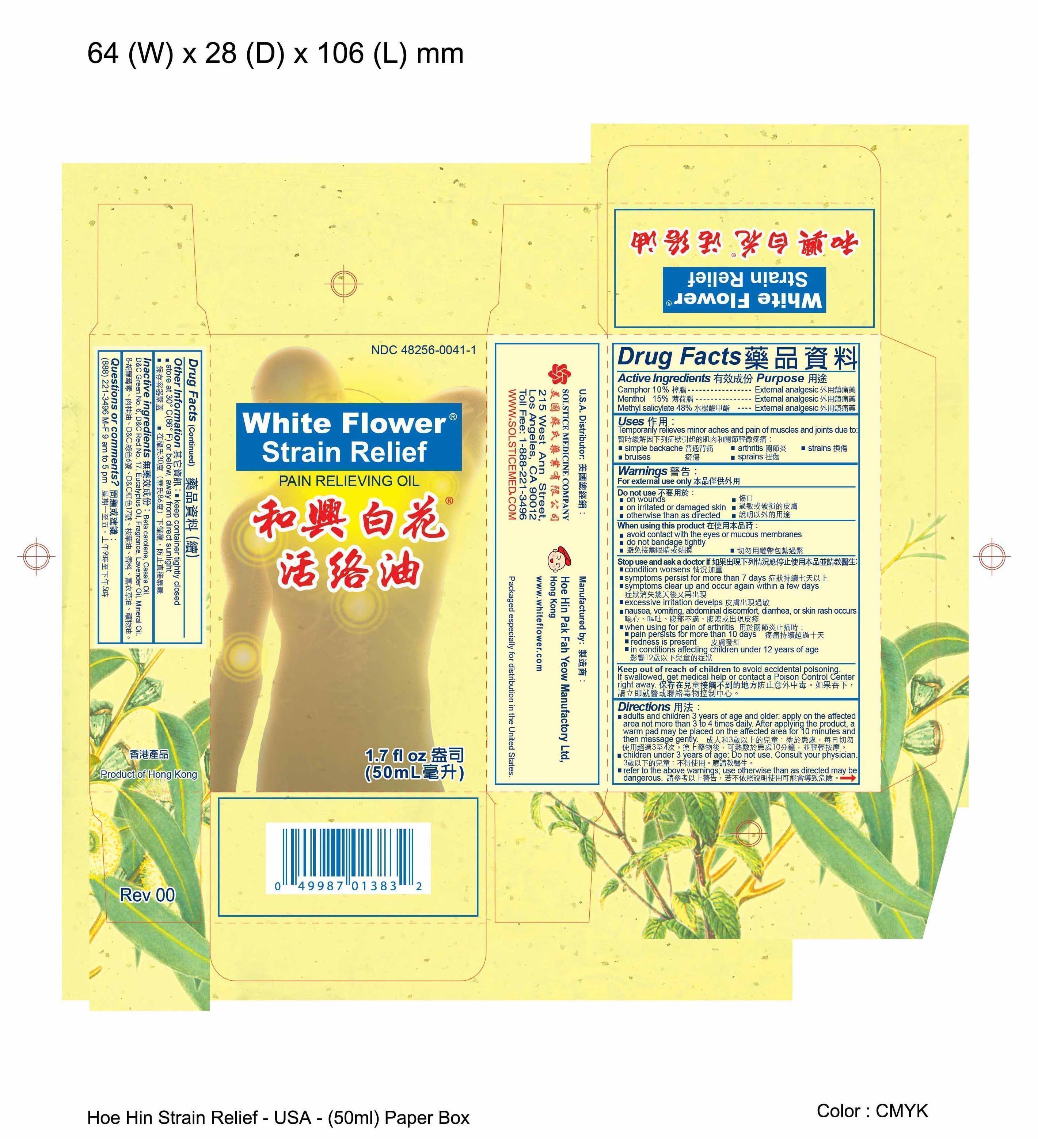 DRUG LABEL: WHITE FLOWER STRAIN RELIEF
NDC: 48256-0041 | Form: OIL
Manufacturer: HOE HIN PAK FAH YEOW MANUFACTORY LTD
Category: otc | Type: HUMAN OTC DRUG LABEL
Date: 20231002

ACTIVE INGREDIENTS: CAMPHOR (SYNTHETIC) 10.2 g/100 mL; MENTHOL 15.3 g/100 mL; METHYL SALICYLATE 49.1 g/100 mL
INACTIVE INGREDIENTS: .BETA.-CAROTENE; CHINESE CINNAMON OIL; D&C GREEN NO. 6; D&C RED NO. 17; EUCALYPTUS OIL; LAVENDER OIL; MINERAL OIL

Drug Facts

Active ingredients

Camphor 10%

Menthol 15%

Methyl salicylate 48%

Purpose

External Analgesic

Uses

Tempoarily relieves minor aches and pains of muscles and joints due to:

- simple backache
- arthritis
- strains
- bruises
- sprains

Warnings

For external use only

Do not use

- on wounds
- on irritated or damaged skin
- otherwise than as directed

When using this product

- avoid contact with the eyes or mucous membranes
- do not bandage tightly

Stop use and ask a doctor if

- condition worsens
- symptoms persis for more than 7 days
- symptoms clear up and occur again within a few days
- excessive irritation develops
- nausea, vomiting, abdominal discomfort, diarrhea, or skin rash occurs
- when using for pain of arthritis:
- pain persists for more than 10 days
- redness is present
- in conditions affecting children under 12 years of age

Keep out of reach of children to avoid accidental poisoning.

If swallowed, get medical help or contact a Poison Control Center right away.

Directions

- adults and children 3 years of age and older: apply on the affected area not more than 3 to 4 times daily. After applying the product, a warm pad may be placed on the affected area for 10 minutes and then massage gently.
- children under 3 years of age: do not use, consult your physician
- refer to the above warnings; use otherwise than as directed may be dangerous

Other information

- store at 30º C (86º F) or below, away from direct sunlight.
- keep container tightly closed

Inactive ingredients

Beta carotene, Cassia oil, D C Green No. 6, D C Red No. 17, Eucalyptus oil, Fragrance, Lavender oil, Mineral oil.

Questions or comments?

(888) 221-3496 M-F 9 am to 5 pm

PACKAGE LABEL

WHITE FLOWER STRAIN RELIEF PAIN RELIEVING OIL NDC 48256-0041-1 1.7 FL OZ (50 ML)